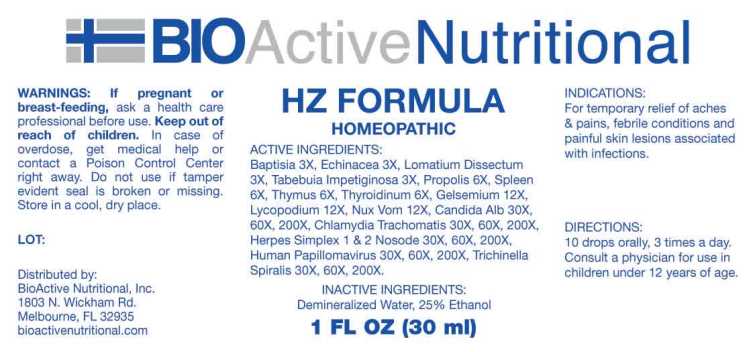 DRUG LABEL: HZ Formula
NDC: 43857-0313 | Form: LIQUID
Manufacturer: BioActive Nutritional, Inc
Category: homeopathic | Type: HUMAN OTC DRUG LABEL
Date: 20240829

ACTIVE INGREDIENTS: BAPTISIA TINCTORIA WHOLE 3 [hp_X]/1 mL; ECHINACEA ANGUSTIFOLIA WHOLE 3 [hp_X]/1 mL; LOMATIUM DISSECTUM ROOT 3 [hp_X]/1 mL; TABEBUIA IMPETIGINOSA BARK 3 [hp_X]/1 mL; PROPOLIS WAX 6 [hp_X]/1 mL; SUS SCROFA SPLEEN 6 [hp_X]/1 mL; SUS SCROFA THYMUS 6 [hp_X]/1 mL; THYROID 6 [hp_X]/1 mL; GELSEMIUM SEMPERVIRENS ROOT 12 [hp_X]/1 mL; LYCOPODIUM CLAVATUM SPORE 12 [hp_X]/1 mL; STRYCHNOS NUX-VOMICA SEED 12 [hp_X]/1 mL; CHLAMYDIA TRACHOMATIS 30 [hp_X]/1 mL; HUMAN HERPESVIRUS 1 30 [hp_X]/1 mL; HUMAN HERPESVIRUS 2 30 [hp_X]/1 mL; CANDIDA ALBICANS 30 [hp_X]/1 mL; HUMAN PAPILLOMAVIRUS 30 [hp_X]/1 mL; TRICHINELLA SPIRALIS 30 [hp_X]/1 mL
INACTIVE INGREDIENTS: WATER; ALCOHOL

DRUG FACTS:

ACTIVE INGREDIENTS:

Baptisia Tinctoria 3X, Echinacea (Angustifolia) 3X, Lomatium Dissectum 3X, Tabebuia Impetiginosa 3X, Propolis 6X, Spleen (suis) 6X, Thymus (suis) 6X, Thyroidinum (suis) 6X, Gelsemium Sempervirens 12X, Lycopodium Clavatum 12X, Nux Vomica 12X, Chlamydia Trachomatis 30X, 60X, 200X, Herpes I 30X, 60X, 200X, Herpes II 30X, 60X, 200X, Candida Albicans 30X, 60X, 200X, Human Papilloma Virus 30X, 60X, 200X, Trichinella Spiralis 30X, 60X, 200X.

INDICATIONS:

For temporary relief of aches and pains, febrile conditions and painful skin lesions associated with infections.

WARNINGS:

If pregnant or breast-feeding, ask a health care professional before use.

Keep out of reach of children. In case of overdose, get medical help or contact a Poison Control Center right away.

Do not use if tamper evident seal is broken or missing.

Store in cool, dry place.

Keep out of reach of children. In case of overdose, get medical help or contact a Poison Control Center right away.

DIRECTIONS:

10 drops orally, 3 times a day. Consult a physician for use in children under 12 years of age.

INDICATIONS:

For temporary relief of aches and pains, febrile conditions and painful skin lesions associated with infections.

INACTIVE INGREDIENTS:

Demineralized Water, 25% Ethanol

QUESTIONS:

Distributed by:
BioActive Nutritional, Inc.
1803 N. Wickham Rd.
Melbourne, FL 32935
bioactivenutritional.com

*For a complete list of HZ Nosode contact

BioActive Nutritional, Inc.

PACKAGE LABEL DISPLAY:

BIOActive Nutritional

HZ FORMULA

HOMEOPATHIC

1 FL OZ (30 ml)